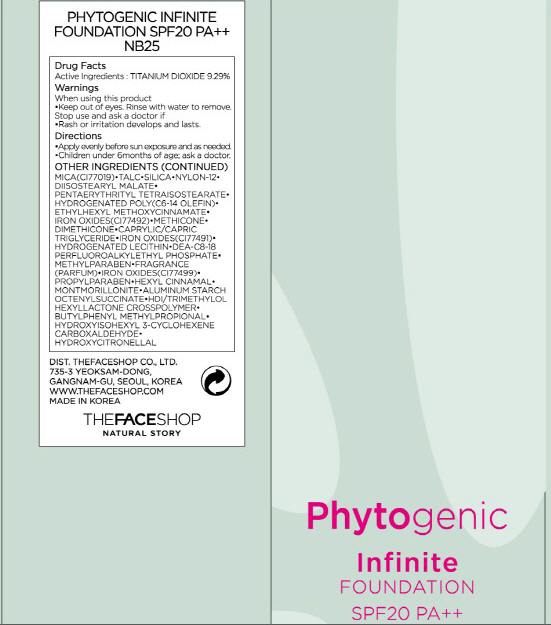 DRUG LABEL: PHYTOGENIC INFINITE FOUNDATION
NDC: 51523-028 | Form: CREAM
Manufacturer: THEFACESHOP CO., LTD.
Category: otc | Type: HUMAN OTC DRUG LABEL
Date: 20100929

ACTIVE INGREDIENTS: TITANIUM DIOXIDE 3.25 mL/35 mL

Drug Facts

Active Ingredient: TITANIUM DIOXIDE

Inactive Ingredients:

WATER, CYCLOPENTASILOXANE, CYCLOHEXASILOXANE, BUTYLENE GLYCOL, PEG-10 DIMETHICONE, IRON OXIDES(CI77492), ORYZA SATIVA (RICE) BRAN OIL,
CAPRYLIC/CAPRIC TRIGLYCERIDE, DIMETHICONE, GLYCERIN, DISTEARDIMONIUM HECTORITE, MAGNESIUM SULFATE, SORBITAN SESQUIOLEATE, HEXYL LAURATE,
IRON OXIDES(CI77491), CETYL PEG/PPG-10/1 DIMETHICONE, DIMETHICONE/VINYL DIMETHICONE CROSSPOLYMER, TRIETHOXYCAPRYLYLSILANE, METHYLPARABEN, CHLORPHENESIN, TRIHYDROXYSTEARIN, IRON OXIDES(CI77499), ALUMINUM HYDROXIDE, CALCIUM STEARATE, FRAGRANCE, STEARIC ACID, METHYL METHACRYLATE CROSSPOLYMER, BETA GLUCAN, PROPYLPARABEN, CAMELLIA SINENSIS LEAF EXTRACT, PORTULACA OLERACEA EXTRACT, DISODIUM EDTA, DIOSPYROS KAKI LEAF EXTRACT, HYDROXYISOHEXYL 3-CYCLOHEXENE CARBOXALDEHYDE, LIMONENE, HONEY EXTRACT, GINKGO BILOBA LEAF EXTRACT, PHENOXYETHANOL

Warnings:
When using this product
Keep out of eyes. Rinse with water to remove.
Stop use and ask a doctor if
Rash or irritation develops and lasts.
Directions:
Apply evenly before sun exposure and as needed.
Children under 6months of age; ask a doctor.